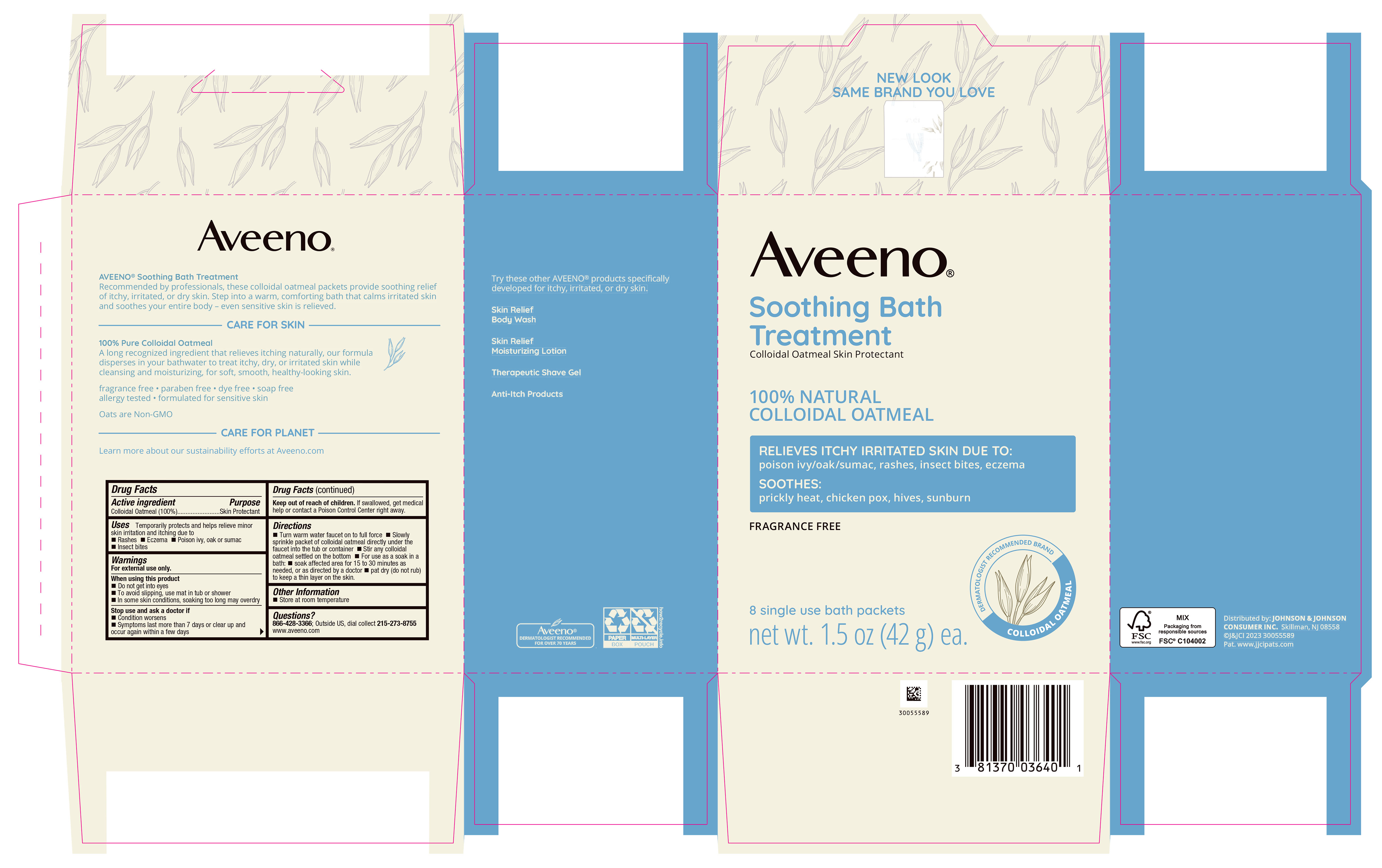 DRUG LABEL: Aveeno Soothing Bath Treatment
NDC: 69968-0405 | Form: POWDER
Manufacturer: Kenvue Brands LLC
Category: otc | Type: HUMAN OTC DRUG LABEL
Date: 20250725

ACTIVE INGREDIENTS: OATMEAL 1000 mg/1 g

Aveeno® SOOTHING BATH TREATMENT

Drug Facts

Active ingredient

Colloidal Oatmeal (100%)

Purpose

Skin Protectant

Uses

Temporarily protects and helps relieve minor skin irritation and itching due to

- Rashes
- Eczema
- Poison ivy, oak or sumac
- Insect bites

Warnings

For external use only.

When using this product

- Do not get into eyes
- To avoid slipping, use mat in tub or shower
- In some skin conditions, soaking too long may overdry

Stop use and ask a doctor if

- Condition worsens
- Symptoms last more than 7 days or clear up and occur again within a few days.

Keep out of reach of children. If swallowed, get medical help or contact a Poison Control Center right away.

Directions

- Turn warm water faucet on to full force
- Slowly sprinkle packet of colloidal oatmeal directly under the faucet into the tube or container
- Stir any colloidal oatmeal settled on the bottom
- For use as a soak in a bath:
  - soak affected area for 15 to 30 minutes as needed, or as directed by a doctor
  - pat dry (do not rub) to keep a thin layer on the skin.

Other information

- Store at room temperature

Questions?

866-428-3366; Outside US, dial collect 215-273-8755 www.aveeno.com

Distributed by:
JOHNSON & JOHNSON
CONSUMER INC.
Skillman, NJ 08558

PRINCIPAL DISPLAY PANEL - 42 g Packet Carton

Aveeno®

Soothing Bath

Treatment

Colloidal Oatmeal Skin Protectant

100% NATURAL

COLLOIDAL OATMEAL

RELIEVES ITCHY IRRITATED SKIN DUE TO:

poison ivy/oak/sumac, rashes, insect bites, eczema

SOOTHES:

prickly heat, chicken pox, hives, sunburn

FRAGRANCE FREE

DERMATOLOGIST RECOMMENDED BRAND

COLLOIDAL OATMEAL

8 single use bath packets

net wt. 1.5 oz (42 g) ea.